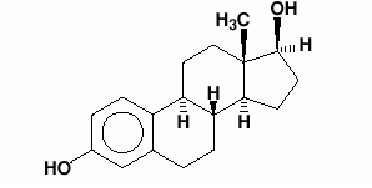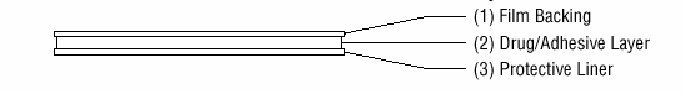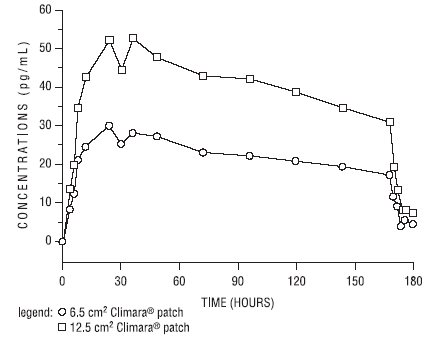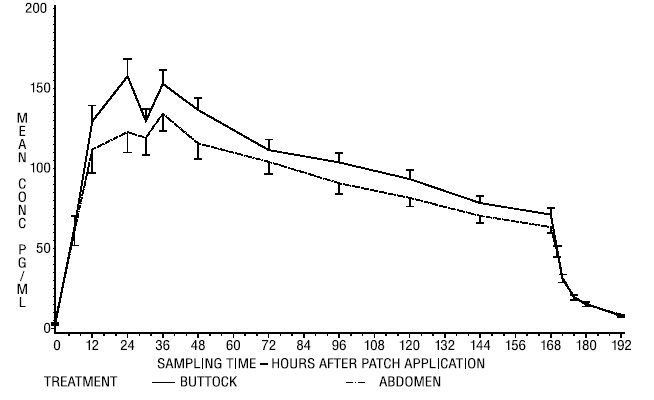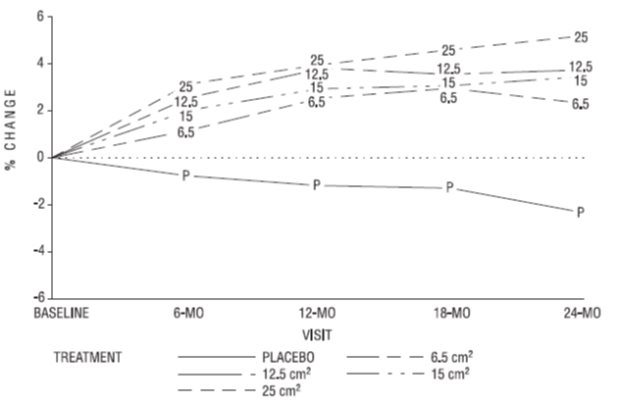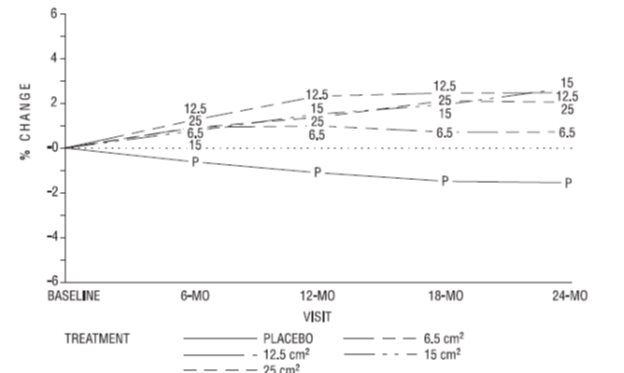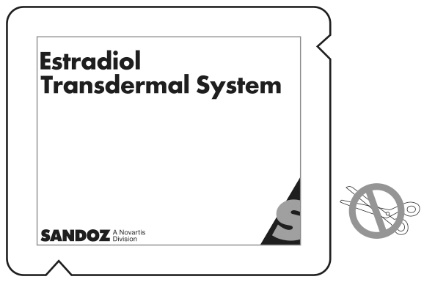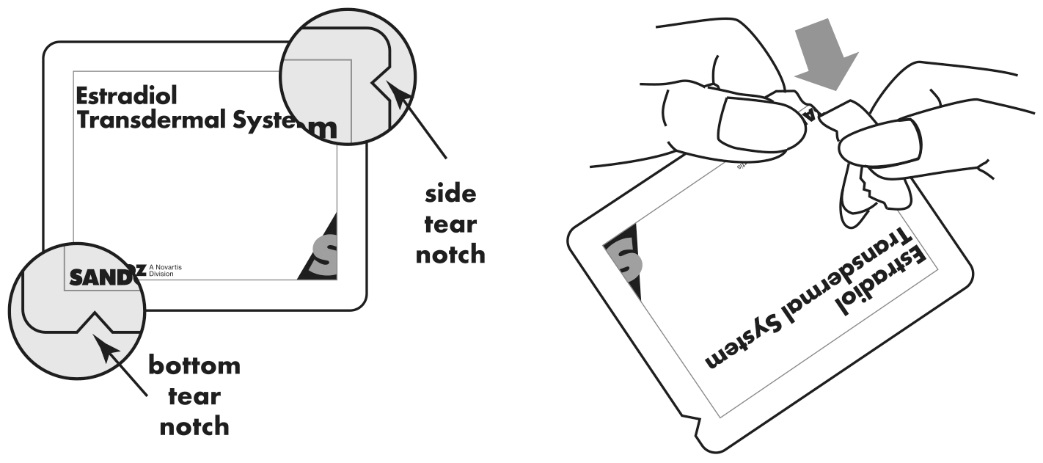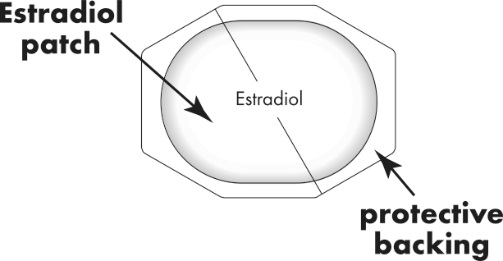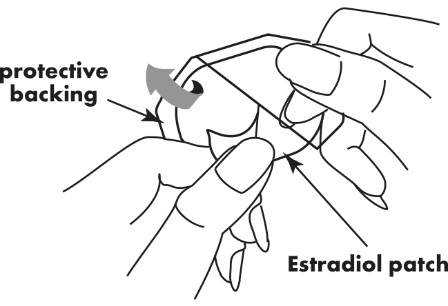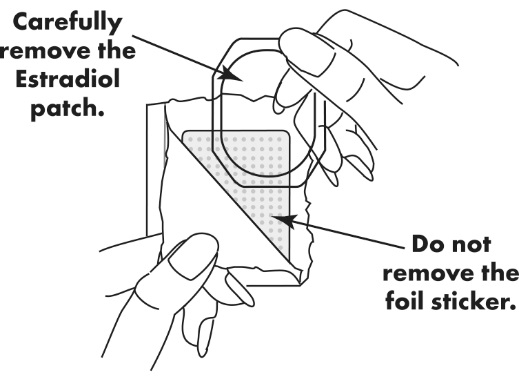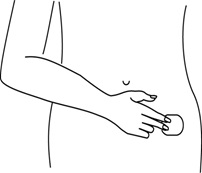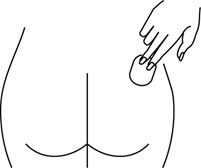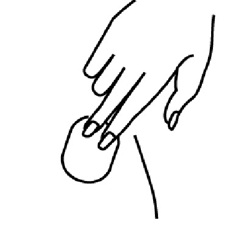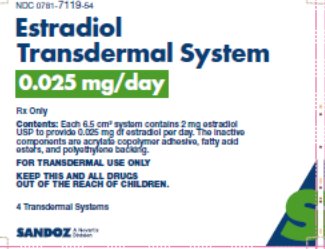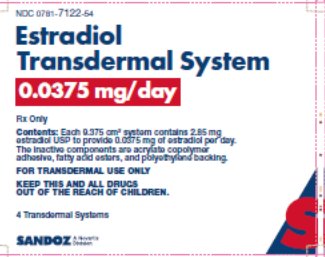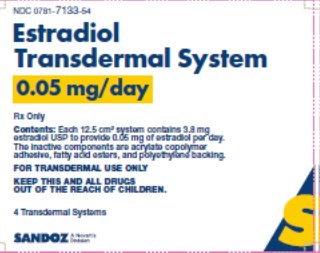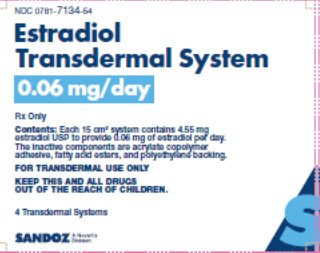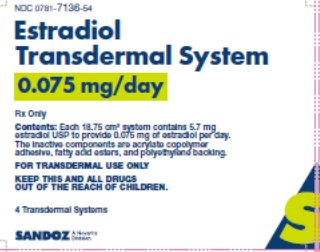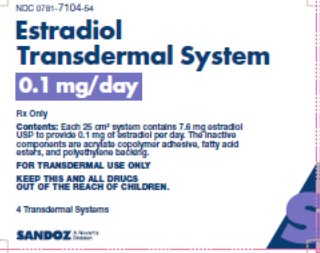 DRUG LABEL: Estradiol Transdermal System
NDC: 59368-421 | Form: PATCH
Manufacturer: Praxis, LLC
Category: prescription | Type: HUMAN PRESCRIPTION DRUG LABEL
Date: 20230101

ACTIVE INGREDIENTS: ESTRADIOL 0.025 mg/1 d

Estradiol Transdermal System

8 USE IN SPECIFIC POPULATIONS

8.1 Pregnancy

Risk Summary

the Estradiol Transdermal System is not indicated for use in pregnancy. There are no data with the use of the Estradiol Transdermal System in pregnant women; however, epidemiologic studies and meta-analyses have not found an increased risk of genital or nongenital birth defects (including cardiac anomalies and limb-reduction defects) following exposure to combined hormonal contraceptives (estrogens and progestins) before conception or during early pregnancy.

In the U.S. general population, the estimated background risk of major birth defects and miscarriage in clinically recognized pregnancies is 2% to 4% and 15% to 20%, respectively.

8.2 Lactation

Risk Summary

Estrogens are present in human milk and can reduce milk production in breast-feeding women. This reduction can occur at any time but is less likely to occur once breast-feeding is well-established. The developmental and health benefits of breastfeeding should be considered along with the mother’s clinical need for the Estradiol Transdermal System and any potential adverse effects on the breastfed child from the Estradiol Transdermal System or from the underlying maternal condition.

8.4 Pediatric Use

In general, the Estradiol Transdermal System is not indicated for use in pediatric patients. Clinical studies have not been conducted in the pediatric population.

If estrogen is administered to patients whose bone growth is not complete, periodic monitoring of bone metabolism and effects on epiphyseal centers is recommended during estrogen administration.

8.5 Geriatric Use

There have not been sufficient numbers of geriatric women involved in clinical studies utilizing the Estradiol Transdermal System to determine whether those over 65 years of age differ from younger subjects in their response to the Estradiol Transdermal System.

The Women’s Health Initiative Studies

In the WHI estrogen-alone substudy (daily CE [0.625 mg]-alone versus placebo), there was a higher relative risk of stroke in women greater than 65 years of age [see Clinical Studies (14.3)] .

In the WHI estrogen plus progestin substudy (daily CE [0.625 mg] plus MPA [2.5 mg] versus placebo), there was a higher relative risk of nonfatal stroke and invasive breast cancer in women greater than 65 years of age [see Clinical Studies (14.3)] .

The Women’s Health Initiative Memory Study

In the WHIMS ancillary studies of postmenopausal women 65 to 79 years of age, there was an increased risk of developing probable dementia in women receiving estrogen-alone or estrogen plus progestin when compared to placebo [see Warnings and Precautions (5.3), and Clinical Studies (14.4)] .

Since both ancillary studies were conducted in women 65 to 79 years of age, it is unknown whether these findings apply to younger postmenopausal women^8 [see Warnings and Precautions (5.3), and Clinical Studies (14.4)] .

10 OVERDOSAGE

Overdosage of estrogen may cause nausea, vomiting, breast tenderness, abdominal pain, drowsiness and fatigue, and withdrawal bleeding in women. Treatment of overdose consists of discontinuation of the Estradiol Transdermal System therapy with institution of appropriate symptomatic care.

11 DESCRIPTION

The Estradiol Transdermal System (estradiol transdermal system), is designed to release estradiol continuously upon application to intact skin. Six (6.5, 9.375, 12.5, 15, 18.75 and 25 cm^2) systems are available to provide nominal in vivodelivery of 0.025, 0.0375, 0.05, 0.06, 0.075 or 0.1 mg respectively of estradiol per day. The period of use is 7 days. Each system has a contact surface area of either 6.5, 9.375, 12.5, 15, 18.75 or 25 cm^2, and contains 2, 2.85, 3.8, 4.55, 5.7 or 7.6 mg of estradiol USP respectively. The composition of the systems per unit area is identical.

Estradiol USP is a white, crystalline powder, chemically described as estra-1,3,5(10)-triene-3, 17β-diol. It has an empirical formula of C18H24O2and molecular weight of 272.38. The structural formula is:

The Estradiol Transdermal System transdermal system comprises three layers. Proceeding from the visible surface toward the surface attached to the skin, these layers are:

1. A translucent polyethylene film.
2. An acrylate adhesive matrix containing estradiol USP.
3. A protective liner of siliconized or fluoropolymer-coated polyester film is attached to the adhesive surface and must be removed before the system can be used.

The active component of the transdermal system is estradiol. The remaining components of the transdermal system (acrylate copolymer adhesive, fatty acid esters, and polyethylene backing) are pharmacologically inactive.

12 CLINICAL PHARMACOLOGY

12.1 Mechanism of Action

Endogenous estrogens are largely responsible for the development and maintenance of the female reproductive system and secondary sexual characteristics. Although circulating estrogens exist in a dynamic equilibrium of metabolic interconversions, estradiol is the principal intracellular human estrogen and is substantially more potent than its metabolites, estrone and estriol at the receptor level.

The primary source of estrogen in normally cycling adult women is the ovarian follicle, which secretes 70 to 500 mcg of estradiol daily, depending on the phase of the menstrual cycle. After menopause, most endogenous estrogen is produced by conversion of androstenedione, which is secreted by the adrenal cortex, to estrone in the peripheral tissues. Thus, estrone and the sulfate conjugated form, estrone sulfate, are the most abundant circulating estrogens in postmenopausal women.

Estrogens act through binding to nuclear receptors in estrogen-responsive tissues. To date, two estrogen receptors have been identified. These vary in proportion from tissue to tissue.

Circulating estrogens modulate the pituitary secretion of the gonadotropins, luteinizing hormone (LH) and FSH, through a negative feedback mechanism. Estrogens act to reduce the elevated levels of these hormones seen in postmenopausal women.

12.2 Pharmacodynamics

Generally, a serum estrogen concentration does not predict an individual woman’s therapeutic response to the Estradiol Transdermal System nor her risk for adverse outcomes. Likewise, exposure comparisons across different estrogen products to infer efficacy or safety for the individual woman may not be valid.

12.3 Pharmacokinetics

Absorption

Transdermal administration of the Estradiol Transdermal System produces mean serum concentrations of estradiol comparable to those produced by premenopausal women in the early follicular phase of the ovulatory cycle. The pharmacokinetics of estradiol following application of the Estradiol Transdermal System transdermal system were investigated in 197 healthy postmenopausal women in six studies. In five of the studies, the Estradiol Transdermal System transdermal system was applied to the abdomen, and in a sixth study, application to the buttocks and abdomen were compared.

The Estradiol Transdermal System transdermal delivery system continuously releases estradiol which is transported across intact skin leading to sustained circulating levels of estradiol during a 7-day treatment period. The systemic availability of estradiol after transdermal administration is about 20 times higher than that after oral administration. This difference is due to the absence of first pass metabolism when estradiol is given by the transdermal route.

In a bioavailability study, the Estradiol Transdermal System 6.5 cm^2was studied with the Estradiol Transdermal System 12.5 cm^2as reference. The mean estradiol levels in serum from the two sizes are shown in Figure 1.

Dose proportionality was demonstrated for the Estradiol Transdermal System 6.5 cm^2as compared to the Estradiol Transdermal System 12.5 cm^2in a 2-week crossover study with a 1-week washout period between the two-transdermal systems in 24 postmenopausal women.

Dose proportionality was also demonstrated for the Estradiol Transdermal System (12.5 cm^2and 25 cm^2) in a 1-week study conducted in 54 postmenopausal women. The mean steady state levels (Cavg) of the estradiol during the application of the Estradiol Transdermal System 25 cm^2and 12.5 cm^2on the abdomen were about 80 and 40 pg/mL, respectively.

In a 3-week multiple application study in 24 postmenopausal women, the 25 cm^2Estradiol Transdermal System produced average peak estradiol concentrations (Cmax) of approximately 100 pg/mL. Trough values at the end of each wear interval (Cmin) were approximately 35 pg/mL. Nearly identical serum curves were seen each week, indicating little or no accumulation of estradiol in the body. Serum estrone peak and trough levels were 60 and 40 pg/mL, respectively.

In a single dose, randomized, crossover study conducted to compare the effect of site of application, 38 postmenopausal women wore a single Estradiol Transdermal System 25 cm^2transdermal system for 1 week on the abdomen and buttocks. The estradiol serum concentration profiles are shown in Figure 2. Values of Cmaxand Cavgwere, respectively, 25 percent and 17 percent higher with the buttock application than with the abdomen application.

Table 2 provides a summary of estradiol pharmacokinetic parameters determined during evaluation of the Estradiol Transdermal System transdermal system.

Table 2: Pharmacokinetic Summary (Mean Estradiol Values)
Estradiol Transdermal System Delivery Rate | Surface Area (cm^2) | Application Site | No. of Subjects | Dosing | Cmax (pg/mL) | Cmin (pg/mL) | Cavg (pg/mL)
0.025 | 6.5 | Abdomen | 24 | Single | 32 | 17 | 22
0.05 | 12.5 | Abdomen | 102 | Single | 71 | 29 | 41
0.1 | 25 | Abdomen | 139 | Single | 147 | 60 | 87
0.1 | 25 | Buttock | 38 | Single | 174 | 71 | 106

The relative standard deviation of each pharmacokinetic parameter after application to the abdomen averaged 50 percent, which is indicative of the considerable intersubject variability associated with transdermal drug delivery. The relative standard deviation of each pharmacokinetic parameter after application to the buttock was lower than that after application to the abdomen (for example, for Cmax39 percent versus 62 percent, and for Cavg35 percent versus 48 percent).

Distribution

The distribution of exogenous estrogens is similar to that of endogenous estrogens. Estrogens are widely distributed in the body and are generally found in higher concentrations in the sex hormone target organs. Estrogens circulate in the blood largely bound to SHBG and albumin.

Metabolism

Exogenous estrogens are metabolized in the same manner as endogenous estrogens. Circulating estrogens exist in a dynamic equilibrium of metabolic interconversions. These transformations take place mainly in the liver. Estradiol is converted reversibly to estrone, and both can be converted to estriol, which is a major urinary metabolite. Estrogens also undergo enterohepatic recirculation via sulfate and glucuronide conjugation in the liver, biliary secretion of conjugates into the intestine, and hydrolysis in the intestine followed by reabsorption. In postmenopausal women, a significant proportion of the circulating estrogens exist as sulfate conjugates, especially estrone sulfate, which serves as a circulating reservoir for the formation of more active estrogens.

Excretion

Estradiol, estrone, and estriol are excreted in the urine along with glucuronide and sulfate conjugates.

Adhesion

An open-label study of adhesion potentials of placebo transdermal systems that correspond to the 6.5 cm^2and 12.5 cm^2sizes of the Estradiol Transdermal System was conducted in 112 healthy women of 45 to 75 years of age. Each woman applied both transdermal systems weekly, on the upper outer abdomen, for 3 consecutive weeks. It should be noted that lower abdomen and upper quadrant of the buttock are the approved sites of application for the Estradiol Transdermal System.

The adhesion assessment was done visually on Days 2, 4, 5, 6, 7 of each week of transdermal system wear. A total of 1,654 adhesion observations were conducted for 333 transdermal systems of each size.

Of these observations, approximately 90 percent showed essentially no lift for both the 6.5 cm^2and 12.5 cm^2transdermal systems. Of the total number of transdermal systems applied, approximately 5 percent showed complete detachment for each size. Adhesion potentials of the 18.75 cm^2and 25 cm^2sizes of transdermal systems (0.075 mg per day and 0.1 mg per day) have not been studied.

13 NONCLINICAL TOXICOLOGY

13.1 Carcinogenesis, Mutagenesis, Impairment of Fertility

Long-term continuous administration of natural and synthetic estrogens in certain animal species increases the frequency of carcinomas of the breast, uterus, cervix, vagina, testis, and liver.

14 CLINICAL STUDIES

14.1 Effects on Vasomotor Symptoms in Postmenopausal Women

A study of 214 women 25 to 74 years of age met the qualification criteria and were randomly assigned to one of the three treatment groups: 72 to the 0.05 mg estradiol patch, 70 to the 0.1 mg estradiol patch, and 72 to placebo. Potential participants were postmenopausal women in good general health who experienced vasomotor symptoms. Natural menopause patients had not menstruated for at least 12 months and surgical menopause patients had undergone bilateral oophorectomy at least 4 weeks before evaluation for study entry. In order to enter the 11-week treatment phase of the study, potential participants must have experienced a minimum of five moderate to severe hot flushes per week, or a minimum of 15 hot flushes of any severity per week, for 2 consecutive weeks. Women wore the patches in a cyclical fashion (three weeks on and one week off).

During treatment, all women used diaries to record the number and severity of hot flushes. Women were monitored by clinic visits at the end of weeks 1, 3, 7, and 11 and by telephone at the end of weeks 4, 5, 8, and 9.

Adequate data for the analysis of efficacy was available from 191 subjects. The results are presented as the mean ± SD number of flushes in each of the 3 treatment weeks of each 4-week cycle. In the 0.05 mg estradiol group, the mean weekly hot flush rate across all treatment cycles decreased from 46 ± 6.5 at baseline to 20 ± 3 (-67 percent). The 0.1 mg estradiol group had a decline in the mean weekly hot flush rate from 52 ± 4.4 at baseline to 16 ± 2.4 (-72 percent). In the placebo group, the mean weekly hot flush rate declined from 53 ± 4.5 at baseline to 46 ± 6.5 (-18.1 percent). Compared with placebo, the 0.05 mg and 0.1 mg estradiol groups showed a statistically significantly larger mean decrease in hot flushes across all treatment cycles (P<0.05). When the response to treatment was analyzed for each of the three cycles of therapy, similar statistically significant differences were observed between both estradiol treatment groups and the placebo group during all treatment cycles.

In a double-blind, placebo-controlled, randomized study of 187 women receiving estradiol 0.025 mg per day or placebo continuously for up to three 28-day cycles, the estradiol 0.025 mg per day dosage was shown to be statistically better than placebo at weeks 4 and 12 for relief of both the frequency and severity of moderate to severe vasomotor symptoms.

Table 3: Mean Change from Baseline in the Number of Moderate to Severe Vasomotor Symptoms Intent to Treat (ITT)
Treatment Group | Statistics | Week 4 | Week 8 | Week 12
E2Transdermal System | N | 82 | 84 | 68
 | Mean | -6.45 | -7.69 | -7.56
 | SD | 4.65 | 4.76 | 4.64
Placebo | N | 83 | 71 | 65
Placebo | Mean | -5.11 | -5.98 | -5.98
Placebo | SD | 7.43 | 8.63 | 9.69
Placebo | p-value | <0.002 |  | <0.003

A second active-control trial of 193 randomized women was supportive of the placebo-controlled trial.

14.2 Effects on Bone Mineral Density in Postmenopausal Women

A two-year clinical trial enrolled a total of 175 healthy, hysterectomized, postmenopausal, non-osteoporotic (that is, lumbar spine bone mineral density >0.9 gm/cm^2) women at 10 study centers in the United States. A total of 129 participating women were allocated to receive active treatment with 4 different doses of estradiol patches (6.5, 12.5, 15, 25 cm^2) and 46 participating women were allocated to receive placebo patches. Seventy-seven percent of the randomized women (100 on active drug and 34 on placebo) contributed data to the analysis of percent change of anterior-posterior (A-P) spine BMD, the primary efficacy variable (see Figure 3). A statistically significant overall treatment effect at each timepoint was noted, implying bone preservation for all active treatment groups at all timepoints, as opposed to bone loss for placebo at all timepoints.

Figure 3: Mean Percent Change from Baseline in Lumbar Spine (A-P View) Bone Mineral Density By Treatment and Time Last Observation Carried Forward

Percent change in BMD of the total hip (see Figure 4) was also statistically significantly different from placebo for all active treatment groups. This figure is based on 74 percent of the randomized women (95 on active drug and 34 on placebo).

14.3 Women's Health Initiative Studies

The WHI enrolled approximately 27,000 predominantly healthy postmenopausal women in two substudies to assess the risks and benefits of daily oral CE (0.625 mg)-alone or in combination with MPA (2.5 mg) compared to placebo in the prevention of certain chronic diseases. The primary endpoint was the incidence of CHD (defined as nonfatal MI, silent MI and CHD death), with invasive breast cancer as the primary adverse outcome. A "global index" included the earliest occurrence of CHD, invasive breast cancer, stroke, PE, endometrial cancer (only in the CE plus MPA substudy), colorectal cancer, hip fracture, or death due to other causes. These substudies did not evaluate the effects of CE-alone or CE plus MPA on menopausal symptoms.

WHI Estrogen-Alone Substudy

The WHI estrogen-alone substudy was stopped early because an increased risk of stroke was observed, and it was deemed that no further information would be obtained regarding the risk and benefits of estrogen-alone in predetermined primary endpoints.

Results of the estrogen-alone substudy, which included 10,739 women (average 63 years of age, range 50 to 79: 75.3 percent White, 15.1 percent Black, 6.1 percent Hispanic, 3.6 percent Other) after an average follow-up of 7.1 years, are presented in Table 4.

Table 4: Relative and Absolute Risk Seen in the Estrogen-Alone Substudy of WHI [Adapted from numerous WHI publications. WHI publications can be viewed at www.nhlbi.nih.gov/whi]
Event | Relative Risk CE vs. Placebo (95% nCI [Nominal confidence intervals unadjusted for multiple looks and multiple comparisons.]) | CE n = 5,310 | Placebo n = 5,429
Event | Relative Risk CE vs. Placebo (95% nCI [Nominal confidence intervals unadjusted for multiple looks and multiple comparisons.]) | Absolute Risk per 10,000 Women-years
CHD events | 0.95 (0.78-1.16) | 54 | 57
Non-fatal MIc | 0.91 (0.73-1.14) | 40 | 43
- CHD death [Results are based on centrally adjudicated data for an average follow-up of 7.1 years.] | 1.01 (0.71-1.43) | 16 | 16
All strokes | 1.33 (1.05-1.68) | 45 | 33
- Ischemic stroke | - 1.55 (1.19-2.01) | - 38 | - 25
Deep vein thrombosis , [Not included in "global index".] | 1.47 (1.06-2.06) | 23 | 15
Pulmonary embolism | 1.37 (0.9-2.07) | 14 | 10
Invasive breast cancer | 0.80 (0.62-1.04) | 28 | 34
Colorectal cancer | 1.08 (0.75-1.55) | 17 | 16
Hip fracture | 0.65 (0.45-0.94) | 12 | 19
Vertebral fractures , | 0.64 (0.44-0.93) | 11 | 18
Lower arm/wrist fractures , | 0.58 (0.47-0.72) | 35 | 59
Total fractures , | 0.71 (0.64-0.80) | 144 | 197
Death due to causes [Results are based on an average follow-up of 6.8 years.] , [All deaths, except from breast or colorectal cancer, definite or probable CHD, PE or cerebrovascular disease.] | 1.08 (0.88-1.32) | 53 | 50
Overall mortality , | 1.04 (0.88-1.22) | 79 | 75
Global Index [A subset of the events was combined in a "global index", defined as the earliest occurrence of CHD events, invasive breast cancer, stroke, pulmonary embolism, endometrial cancer, colorectal cancer, hip fracture, or death due to other causes.] | 1.02 (0.92-1.13) | 206 | 201

For those outcomes included in the WHI "global index" that reached statistical significance, the absolute excess risks per 10,000 women-years in the group treated with CE-alone was 12 more strokes, while the absolute risk reduction per 10,000 women-years was 7 fewer hip fractures.^9The absolute excess risk of events included in the "global index" was a non-significant 5 events per 10,000 women-years. There was no difference between the groups in terms of all-cause mortality.

No overall difference for primary CHD events (nonfatal MI, silent MI and CHD death) and invasive breast cancer incidence in women receiving CE-alone compared with placebo was reported in final centrally adjudicated results from the estrogen-alone substudy, after an average follow-up of 7.1 years. See Table 4.

Centrally adjudicated results for stroke events from the estrogen-alone substudy, after an average follow-up of 7.1 years, reported no significant difference in the distribution of stroke subtype and severity, including fatal strokes, in women receiving estrogen-alone compared to placebo. Estrogen-alone increased the risk of ischemic stroke, and this excess risk was present in all subgroups of women examined.^10See Table 4.

Timing of initiation of estrogen-alone therapy relative to the start of menopause may affect the overall risk-benefit profile. The WHI estrogen-alone substudy stratified by age showed in women 50 to 59 years of age a non-significant trend toward reduced risk for CHD [hazard ratio (HR) 0.63 (95 percent CI, 0.36-1.09)]and overall mortality [HR 0.71 (95 percent CI, 0.46-1.11)].

WHI Estrogen Plus Progestin Substudy

The WHI estrogen plus progestin substudy was stopped early. According to the predefined stopping rule, after an average follow-up of 5.6 years of treatment, the increased risk of invasive breast cancer and cardiovascular events exceeded the specified benefits included in the "global index". The absolute excess risk of events included in the “global index” was 19 per 10,000 women-years.

For those outcomes included in the WHI “global index” that reached statistical significance after 5.6 years of follow-up, the absolute excess risks per 10,000 women-years in the group treated with CE plus MPA were 7 more CHD events, 8 more strokes, 10 more PEs, and 8 more invasive breast cancers, while the absolute risk reduction per 10,000 women-years were 6 fewer colorectal cancers and 5 fewer hip fractures.

Results of the CE plus MPA substudy, which included 16,608 women (average 63 years of age, range 50 to 79; 83.9 percent White, 6.5 percent Black, 5.4 percent Hispanic, 3.9 percent Other), are presented in Table 5 . These results reflect centrally adjudicated data after an average follow-up of 5.6 years.

Table 5: Relative and Absolute Risk Seen in the Estrogen Plus Progestin Substudy of WHI at an Average of 5.6 Years
Event | Relative Risk CE/MPA vs. placebo (95% nCI [Nominal confidence intervals unadjusted for multiple looks and multiple comparisons.]) | CE/MPA n = 8,506 | Placebo; n = 8,102
Event |  | Absolute Risk per 10,000 Women-years
CHD events | 1.23 (0.99-1.53) | 41 | 34
- Non-fatal MI | 1.28 (1.00-1.63) | 31 | 25
- CHD death | 1.10 (0.70-1.75) | 8 | 8
All strokes | 1.31 (1.03-1.68) | 33 | 25
- Ischemic stroke | 1.44 (1.09-1.90) | 26 | 18
Deep vein thrombosis [Not included in "global index".] | 1.95 (1.43-2.67) | 26 | 13
Pulmonary embolism | 2.13 (1.45-3.11) | 18 | 8
Invasive breast cancer [Includes metastatic and non-metastatic breast cancer, with the exception of in situ breast cancer.] | 1.24 (1.01-1.54) | 41 | 33
Colorectal cancer | 0.61 (0.42-0.87) | 10 | 16
Endometrial cancer | 0.81 (0.48-1.36) | 6 | 7
Cervical cancer | 1.44 (0.47-4.42) | 2 | 1
Hip fracture | 0.67 (0.47-0.96) | 11 | 16
Vertebral fractures | 0.65 (0.46-0.92) | 11 | 17
Lower arm/wrist fractures | 0.71 (0.59-0.85) | 44 | 62
Total fractures | 0.76 (0.69-0.83) | 152 | 199
Overall mortality [All deaths, except from breast or colorectal cancer, definite or probable CHD, PE or cerebrovascular disease.] | 1.00 (0.83-1.19) | 52 | 52
Global Index [A subset of the events was combined in a "global index", defined as the earliest occurrence of CHD events, invasive breast cancer, stroke, pulmonary embolism, endometrial cancer, colorectal cancer, hip fracture, or death due to other causes.] | 1.13 (1.02-1.25) | 184 | 165
Adapted from numerous WHI publications. WHI publications can be viewed at www.nhlbi.nih.gov/whi. Results are based on centrally adjudicated data.

Timing of initiation of estrogen plus progestin therapy relative to the start of menopause may affect the overall risk benefit profile. The WHI estrogen plus progestin substudy stratified by age showed in women 50 to 59 years of age a non-significant trend toward reduced risk for overall mortality [HR 0.69 (95 percent CI, 0.44-1.07)].

14.4 Women's Health Initiative Memory Study

The WHIMS estrogen-alone ancillary study of WHI enrolled 2,947 predominantly healthy hysterectomized postmenopausal women 65 to 79 years of age and older (45 percent were 65 to 69 years of age; 36 percent were 70 to 74 years of age; 19 percent were 75 years of age and older) to evaluate the effects of daily CE (0.625 mg)-alone on the incidence of probable dementia (primary outcome) compared to placebo.

After an average follow-up of 5.2 years, the relative risk of probable dementia for CE-alone versus placebo was 1.49 (95 percent CI, 0.83-2.66). The absolute risk of probable dementia for CE-alone versus placebo was 37 versus 25 cases per 10,000 women-years. Probable dementia as defined in the study included Alzheimer’s disease (AD), vascular dementia (VaD) and mixed types (having features of both AD and VaD). The most common classification of probable dementia in the treatment group and the placebo group was AD. Since the ancillary study was conducted in women 65 to 79 years of age, it is unknown whether these findings apply to younger postmenopausal women [see Warnings and Precautions (5.3), and Use in Specific Populations (8.5)] .

The WHIMS estrogen plus progestin ancillary study enrolled 4,532 predominantly healthy postmenopausal women 65 years of age and older (47 percent were 65 to 69 years of age; 35 percent were 70 to 74 years of age; and 18 percent were 75 years of age and older) to evaluate the effects of daily CE (0.625 mg) plus MPA (2.5 mg) on the incidence of probable dementia (primary outcome) compared to placebo.

After an average follow-up of 4 years, the relative risk of probable dementia for CE plus MPA versus placebo was 2.05 (95 percent CI, 1.21-3.48). The absolute risk of probable dementia for CE plus MPA versus placebo was 45 versus 22 cases per 10,000 women-years. Probable dementia as defined in the study included AD, VaD and mixed types (having features of both AD and VaD). The most common classification of probable dementia in the treatment group and the placebo group was AD. Since the ancillary study was conducted in women 65 to 79 years of age, it is unknown whether these findings apply to younger postmenopausal women [see Warnings and Precautions (5.3), and Use in Specific Populations (8.5)] .

When data from the two populations were pooled as planned in the WHIMS protocol, the reported overall relative risk for probable dementia was 1.76 (95 percent CI, 1.19-2.60). Differences between groups became apparent in the first year of treatment. It is unknown whether these findings apply to younger postmenopausal women [see Warnings and Precautions (5.3), and Use in Specific Populations (8.5)]

15 REFERENCES

1. Rossouw JE, et al. Postmenopausal Hormone Therapy and Risk of Cardiovascular Disease by Age and Years Since Menopause. JAMA. 2007;297:1465-1477.
2. Hsia J, et al. Conjugated Equine Estrogens and Coronary Heart Disease. Arch Int Med.2006;166:357-365.
3. Curb JD, et al. Venous Thrombosis and Conjugated Equine Estrogen in Women Without a Uterus. Arch Int Med.2006;166:772-780.
4. Cushman M, et al. Estrogen Plus Progestin and Risk of Venous Thrombosis. JAMA.2004;292:1573-1580.
5. Stefanick ML, et al. Effects of Conjugated Equine Estrogens on Breast Cancer and Mammography Screening in Postmenopausal Women With Hysterectomy. JAMA.2006;295:1647-1657.
6. Chlebowski RT, et al. Influence of Estrogen Plus Progestin on Breast Cancer and Mammography in Healthy Postmenopausal Women. JAMA.2003;289:3234-3253.
7. Anderson GL, et al. Effects of Estrogen Plus Progestin on Gynecologic Cancers and Associated Diagnostic Procedures. JAMA.2003;290:1739-1748.
8. Shumaker SA, et al. Conjugated Equine Estrogens and Incidence of Probable Dementia and Mild Cognitive Impairment in Postmenopausal Women. JAMA.2004;291:2947-2958.
9. Jackson RD, et al. Effects of Conjugated Equine Estrogen on Risk of Fractures and BMD in Postmenopausal Women With Hysterectomy: Results From the Women's Health Initiative Randomized Trial. J Bone Miner Res.2006;21:817-828.
10. Hendrix SL, et al. Effects of Conjugated Equine Estrogen on Stroke in the Women's Health Initiative. Circulation.2006;113:2425-2434.

16 HOW SUPPLIED/STORAGE AND HANDLING

16.1 How Supplied

- Estradiol Transdermal System, 0.025 mg/day — each 6.5 cm^2system contains 2 mg of estradiol USP
  Individual Carton of 4 systems NDC 0781-7119-54
- Estradiol Transdermal System, 0.0375 mg/day — each 9.375 cm^2system contains 2.85 mg of estradiol USP
  Individual Carton of 4 systems NDC 0781-7122-54
- Estradiol Transdermal System, 0.05 mg/day — each 12.5 cm^2system contains 3.8 mg of estradiol USP
  Individual Carton of 4 systems ………………NDC 0781-7133-54
- Estradiol Transdermal System, 0.06 mg/day — each 15 cm^2system contains 4.55 mg of estradiol USP
  Individual Carton of 4 systems NDC 0781-7134-54
- Estradiol Transdermal System, 0.075 mg/day — each 18.75 cm^2system contains 5.7 mg of estradiol USP
  Individual Carton of 4 systems……………… NDC 0781-7136-54
- Estradiol Transdermal System, 0.1 mg/day — each 25 cm^2system contains 7.6 mg of estradiol USP
  Individual Carton of 4 systems ……………….NDC 0781-7104-54

16.2 Storage and Handling

Store at 20°C to 25°C (66°F to 77°F); excursions permitted between 15°C and 30°C (59°F and 86°F). Do not store above 86°F (30°C).

Do not store unpouched. Apply immediately upon removal from the protective pouch.

Used transdermal systems still contain active hormone. To discard, fold the sticky side of the transdermal system together, place it in a sturdy child-proof container, and place this container in the trash. Used transdermal systems should not be flushed in the toilet.

17 PATIENT COUNSELING INFORMATION

Advise women to read the FDA-approved patient labeling (Patient Information and Instructions for Use)

Vaginal Bleeding

Inform postmenopausal women to report any vaginal bleeding to their healthcare provider as soon as possible [see Warning and Precautions (5.2)] .

Possible Serious Adverse Reactions with Estrogen-Alone Therapy

Inform postmenopausal women of possible serious adverse reactions of estrogen-alone therapy including Cardiovascular Disorders, Malignant Neoplasms, and Probable Dementia [see Warnings and Precautions (5.1, 5.2, 5.3)].

Possible Common Adverse Reactions with Estrogen-Alone Therapy

Inform postmenopausal women of possible less serious but common adverse reactions of estrogen-alone therapy such as headache, breast pain and tenderness, nausea and vomiting.

Patient Package Insert

Patient Information

Estradiol Transdermal System

Read this Patient Information before you start using Estradiol Transdermal System and each time you get a refill. There may be new information. This information does not take the place of talking to your healthcare provider about your menopausal symptoms or your treatment.

What is the most important information I should know about the Estradiol Transdermal System (an estrogen hormone)?

- Using estrogen-alone may increase your chance of getting cancer of the uterus (womb).
- Report any unusual vaginal bleeding right away while you are using the Estradiol Transdermal System. Vaginal bleeding after menopause may be a warning sign of cancer of the uterus (womb). Your healthcare provider should check any unusual vaginal bleeding to find out the cause.
- Do not use estrogen-alone to prevent heart disease, heart attacks, strokes, or dementia (decline in brain function).
- Using estrogen-alone may increase your chances of getting strokes or blood clots.
- Using estrogen-alone may increase your chance of getting dementia, based on a study of women age 65 years of age and older.
- Do not use estrogens with progestogens to prevent heart disease, heart attacks, strokes or dementia.
- Using estrogens with progestogens may increase your chances of getting heart attacks, strokes, breast cancer, or blood clots.
- Using estrogens with progestogens may increase your chance of getting dementia, based on a study of women age 65 years of age and older.
- Only one estrogen-alone product and dose have been shown to increase your chances of getting strokes, blood clots, and dementia. Only one estrogen with progestogen product and dose have been shown to increase your chances of getting heart attacks, strokes, breast cancer, blood clots, and dementia.
- Because other products and doses have not been studied in the same way, it is not known how the use of the Estradiol Transdermal System will affect your chances of these conditions. You and your healthcare provider should talk regularly about whether you still need treatment with the Estradiol Transdermal System.

What is the Estradiol Transdermal System?

the Estradiol Transdermal System is a prescription medicine patch (transdermal system) that contains estradiol (an estrogen hormone).

What is the Estradiol Transdermal System used for?

The Estradiol Transdermal System is used after menopause to:

- Reduce moderate to severe hot flashes
- Estrogens are hormones made by a woman’s ovaries. The ovaries normally stop making estrogens when a woman is between 45 and 55 years old. This drop in body estrogen levels causes the "change of life" or menopause (the end of monthly menstrual periods). Sometimes, both ovaries are removed during an operation before natural menopause takes place. The sudden drop in estrogen levels causes "surgical menopause."
- When estrogen levels begin dropping, some women develop very uncomfortable symptoms, such as feelings of warmth in the face, neck, and chest, or sudden intense feelings of heat and sweating ("hot flashes" or "hot flushes"). In some women, the symptoms are mild, and they will not need to use estrogens. In other women, symptoms can be more severe.
- Treat moderate to severe menopausal changes in and around the vagina
- You and your healthcare provider should talk regularly about whether you still need treatment with the Estradiol Transdermal System to control these problems. If you use the Estradiol Transdermal System only to treat your menopausal changes in and around your vagina, talk with your healthcare provider about whether a topical vaginal product would be better for you.
- Treat certain conditions in women before menopause if their ovaries do not produce enough estrogens naturally
- Help reduce your chances of getting osteoporosis (thin weak bones)
- Osteoporosis from menopause is a thinning of the bones that makes them weaker and easier to break. If you use the Estradiol Transdermal System only to prevent osteoporosis due to menopause, talk with your healthcare provider about whether a different treatment or medicine without estrogens might be better for you.

You and your healthcare provider should talk regularly about whether you still need treatment with the Estradiol Transdermal System.

Who should not use the Estradiol Transdermal System?

Do not start using the Estradiol Transdermal System if you:

- have unusual vaginal bleeding
- Vaginal bleeding after menopause may be a warning sign of cancer of the uterus (womb). Your healthcare provider should check any unusual vaginal bleeding to find out the cause.
- have been diagnosed with a bleeding disorder
- currently have or have had certain cancers
- Estrogens may increase the chance of getting certain types of cancers, including cancer of the breast or uterus (womb). If you have or have had cancer, talk with your healthcare provider about whether you should use the Estradiol Transdermal System.
- had a stroke or heart attack
- currently have or have had blood clots
- currently have or have had liver problems
- are allergic to the Estradiol Transdermal System or any of the ingredients in it.See the list of ingredients in the Estradiol Transdermal System at the end of this leaflet.

Before you use the Estradiol Transdermal System, tell your healthcare provider about all of your medical conditions, including if you:

- have any unusual vaginal bleeding
- Vaginal bleeding after menopause may be a warning sign of cancer of the uterus (womb). Your healthcare provider should check any unusual vaginal bleeding to find out the cause.
- have any other medical conditions that may become worse while you are using the Estradiol Transdermal System
- Your healthcare provider may need to check you more carefully if you have certain conditions, such as asthma (wheezing), epilepsy (seizures), diabetes, migraine, endometriosis, lupus, angioedema (swelling of face and tongue), or problems with your heart, liver, thyroid, kidneys, or have high calcium levels in your blood.
- are going to have surgery or will be on bed rest.
- Your healthcare provider will let you know if you need to stop using the Estradiol Transdermal System.
- are pregnant or think you may be pregnant.
- the Estradiol Transdermal System is not for pregnant women.
- are breastfeeding
- The hormone in the Estradiol Transdermal System can pass into your breast milk.

Tell your healthcare provider about all the medicines you take,including prescription and over-the-counter medicines, vitamins, and herbal supplements. Some medicines may affect how the Estradiol Transdermal System works. the Estradiol Transdermal System may also affect how your other medicines work. Keep a list of your medicines and show it to your healthcare provider and pharmacist when you get new medicine.

How should I use the Estradiol Transdermal System?

For detailed instructions, see the step-by-step instructions for using the Estradiol Transdermal System at the end of this Patient Information.

- Use the Estradiol Transdermal System exactly as your healthcare provider tells you to use it.
- the Estradiol Transdermal System is for skin use only.
- Change your Estradiol Transdermal System patch 1 time each week or every 7 days.
- Apply your Estradiol Transdermal System patch to a clean, dry area on your lower abdomen or buttocks. This area must be clean, dry, and free of powder, oil or lotion for your patch to stick to your skin.
- Apply your Estradiol Transdermal System patch to a different area of your abdomen or your buttocks each time. Do not use the same application site 2 times in the same week.
- Do not apply the Estradiol Transdermal System to your breasts.
- If you forget to apply a new Estradiol Transdermal System patch, apply a new patch as soon as possible.
- You and your healthcare provider should talk regularly (every 3 to 6 months) about the dose you are using and whether you still need treatment with the Estradiol Transdermal System.

How to Change the Estradiol Transdermal System

- When changing the Estradiol Transdermal System, peel off the used patch slowly from the skin.
- After removal of the Estradiol Transdermal System if any adhesive residue remains on your skin, allow the area to dry for 15 minutes. Then, gently rub the area with an oil-based cream or lotion to remove the adhesive from your skin.
- Apply the new patch to a different area of your abdomen or buttocks. This area must be clean, dry, and free of powder, oil or lotion. Do not use the same site again for at least 1 week after removal of an old patch.

What are the possible side effects of the Estradiol Transdermal System?

Side effects are grouped by how serious they are and how often they happen when you are treated.

Serious, but less common side effects include:

Call your healthcare provider right away if you get any of the following warning signs or any other unusual symptoms that concern you:

- new breast lumps
- unusual vaginal bleeding
- changes in vision or speech
- sudden new severe headaches
- severe pains in your chest or legs with or without shortness of breath, weakness and fatigue

Common side effects of the Estradiol Transdermal System include:

- headache
- breast tenderness or pain
- irregular vaginal bleeding or spotting
- stomach or abdominal cramps, bloating
- nausea and vomiting
- hair loss
- fluid retention
- vaginal yeast infection
- redness and/or irritation at the patch placement site

These are not all the possible side effects of the Estradiol Transdermal System. For more information, ask your healthcare provider or pharmacist. Tell your healthcare provider if you have any side effects that bother you or do not go away.

You may report side effects to FDA at 1-800-FDA-1088. You may report side effects to Bayer Healthcare Pharmaceuticals at 1-888-842-2937.

What can I do to lower my chances of a serious side effect with the Estradiol Transdermal System?

- Talk with your healthcare provider regularly about whether you should continue using the Estradiol Transdermal System.
- If you have a uterus, talk with your healthcare provider about whether the addition of a progestogen is right for you. In general, the addition of a progestogen is generally recommended for a woman with a uterus to reduce the chance of getting cancer of the uterus (womb).
- See your healthcare provider right away if you get vaginal bleeding while using the Estradiol Transdermal System.
- Have a pelvic exam, breast exam and mammogram (breast X-ray) every year unless your healthcare provider tells you something else. If members of your family have had breast cancer or if you have ever had breast lumps or an abnormal mammogram, you may need to have breast exams more often.
- If you have high blood pressure, high cholesterol (fat in the blood), diabetes, are overweight, or if you use tobacco, you may have higher chances for getting heart disease. Ask your healthcare provider for ways to lower your chances of getting heart disease.

How should I store and throw away the used Estradiol Transdermal System?

- Store the Estradiol Transdermal System at room temperature 68°F to 77°F (20°C to 25°C).
- Do not store the Estradiol Transdermal System patches outside of their pouches. Apply immediately upon removal from the protective pouch.
- Used patches still contain estrogen. To throw away the patch, fold the sticky side of the patch together, place it in a sturdy child-proof container, and place this container in the trash. Used patches should not be flushed in the toilet.

Keep the Estradiol Transdermal System and all medicines out of the reach of children.

General information about the safe and effective use of the Estradiol Transdermal System.

Medicines are sometimes prescribed for purposes other than those listed in Patient Information leaflets. Do not use the Estradiol Transdermal System for conditions for which it was not prescribed. Do not give the Estradiol Transdermal patch to other people, even if they have the same symptoms you have. It may harm them.

You can ask your healthcare provider or pharmacist for information about the Estradiol Transdermal System that is written for health professionals.

For more information call the toll free number 1-800-525-8747

What are the ingredients in the Estradiol Transdermal System?

Active ingredient:estradiol

Inactive ingredient:acrylate copolymer adhesive, fatty acid esters, and polyethylene backing.

INSTRUCTIONS FOR USE

Estradiol Transdermal System

Read this Patient Information before you start using the Estradiol Transdermal System and each time you get a refill. There may be new information. This information does not take the place of talking to your healthcare provider about your menopausal symptoms or your treatment.

You will need the following supplies: See Figure A

Figure A

Step 1: Pick the days you will change your Estradiol Transdermal System.

You will need to change your patch 1 time each week or every 7 days.

Step 2. Remove the Estradiol Transdermal System patch from the pouch.

- Remove patch from its protective pouch by tearing at the notch (do not use scissors). See Figure B
- Do not remove your patch from the protective pouch until you are ready to apply it.

Figure B

Step 3. Remove the adhesive liner. See Figure C

- You will see that the Estradiol Transdermal System is an oval shaped clear patch that is attached to a thick, hard-plastic adhesive liner and covered by a clear, plastic film. See Figure C
- To apply your patch you must first remove the protective, clear plastic film that is attached to the clear thicker plastic backing. See Figure D
- There is a silver foil-sticker attached to the inside of the pouch. Do not remove the silver foil sticker from the pouch. See Figure E

Figure C

Figure D

Figure E

Step 4. Placing the patch on your skin.

- Apply the sticky side of the patch to 1 of the areas of skin shown below. See Figure Fand Figure G
- Do not touchthe sticky side of the patch with your fingers.

Figure F

Figure G

Note:

- Avoid the waistline, since clothing and belts may cause the patch to be rubbed off.
- Do not apply the Estradiol Transdermal System to your breasts.
- Only apply the Estradiol Transdermal System to skin that is clean, dry, and free of any powder, oil, or lotion.
- Do not apply the patch to injured, burned, or irritated skin, or areas with skin conditions (such as birth marks, tattoos, or that is very hairy).

Step 5. Press the patch firmly onto your skin.

- Press the patch firmly in place with your fingers for at least 10 seconds
- Rub the edges of the patch to make sure that it will stick to your skin. (See Figure H)

Figure H

Note:

- Contact with water while you are swimming, using a sauna, bathing, or showering may cause the patch to fall off.
- If your patch falls off reapply it. If you cannot reapply the patch, apply a new patch to another area (see Figures F and G), and continue to follow your original application schedule.
- If you stop using your the Estradiol Transdermal System patch or forget to apply a new patch as scheduled, you may have spotting, or bleeding, and your symptoms may come back.

Step 6: Throwing away your used patch.

- When it is time to change your patch, remove the old patch before you apply a new patch.
- To throw away the patch, fold the sticky side of the patch together, place it in a sturdy child-proof container, and place this container in the trash. Do not flush used patches in the toilet.

This Patient Information and Instructions for Use have been approved by the U.S Food and Drug Administration.

Revised 9/2021

s

Sandoz Inc.
Princeton, NJ 08540

PACKAGE/LABEL PRINCIPAL DISPLAY PANEL

- NDC 0781-7119-54
- 4 transdermal systems
- Estradiol Transdermal System
- 0.025 mg/day
- Contents: Each 6.5 cm2 system contains 2 mg estradiol USP to
  provide 0.025 mg of estradiol per day. The inactive components
  are acrylate copolymer adhesive, fatty acid esters, and
  polyethylene backing.
- For transdermal use only.
- Keep this and all drugs out of the reach of children.
- Rx only

PACKAGE/LABEL PRINCIPAL DISPLAY PANEL

- NDC 0781-7122-54
- 4 transdermal systems
- Estradiol Transdermal System
- 0.0375 mg/day
- Contents: Each 9.375 cm2 system contains 2.85 mg estradiol USP to
  provide 0.0375 mg of estradiol per day. The inactive components
  are acrylate copolymer adhesive, fatty acid esters, and
  polyethylene backing.
- For transdermal use only.
- Keep this and all drugs out of the reach of children.
- Rx only

PACKAGE/LABEL PRINCIPAL DISPLAY PANEL

- NDC 0781-7133-54
- 4 transdermal systems
- Estradiol Transdermal System
- 0.05 mg/day
- Contents: Each 12.5 cm2 system contains 3.8 mg estradiol USP to
  provide 0.05 mg of estradiol per day. The inactive components
  are acrylate copolymer adhesive, fatty acid esters, and
  polyethylene backing.
- For transdermal use only.
- Keep this and all drugs out of the reach of children.
- Rx only

PACKAGE/LABEL PRINCIPAL DISPLAY PANEL

- NDC 0781-7134-54
- 4 transdermal systems
- Estradiol Transdermal System
- 0.06 mg/day
- Contents: Each 15 cm2 system contains 4.55 mg estradiol USP to
  provide 0.06 mg of estradiol per day. The inactive components
  are acrylate copolymer adhesive, fatty acid esters, and
  polyethylene backing.
- For transdermal use only.
- Keep this and all drugs out of the reach of children.
- Rx only

PACKAGE/LABEL PRINCIPAL DISPLAY PANEL

- NDC 0781-7136-54
- 4 transdermal systems
- Estradiol Transdermal System
- 0.075 mg/day
- Contents: Each 18.75 cm2 system contains 5.7 mg estradiol USP to
  provide 0.075 mg of estradiol per day. The inactive components
  are acrylate copolymer adhesive, fatty acid esters, and
  polyethylene backing.
- For transdermal use only.
- Keep this and all drugs out of the reach of children.
- Rx only

PACKAGE/LABEL PRINCIPAL DISPLAY PANEL

- NDC 0781-7104-54
- 4 transdermal systems
- Estradiol Transdermal System
- 0.1 mg/day
- Contents: Each 25 cm2 system contains 7.6 mg estradiol USP to
  provide 0.1 mg of estradiol per day. The inactive components
  are acrylate copolymer adhesive, fatty acid esters, and
  polyethylene backing.
- For transdermal use only.
- Keep this and all drugs out of the reach of children.
- Rx only